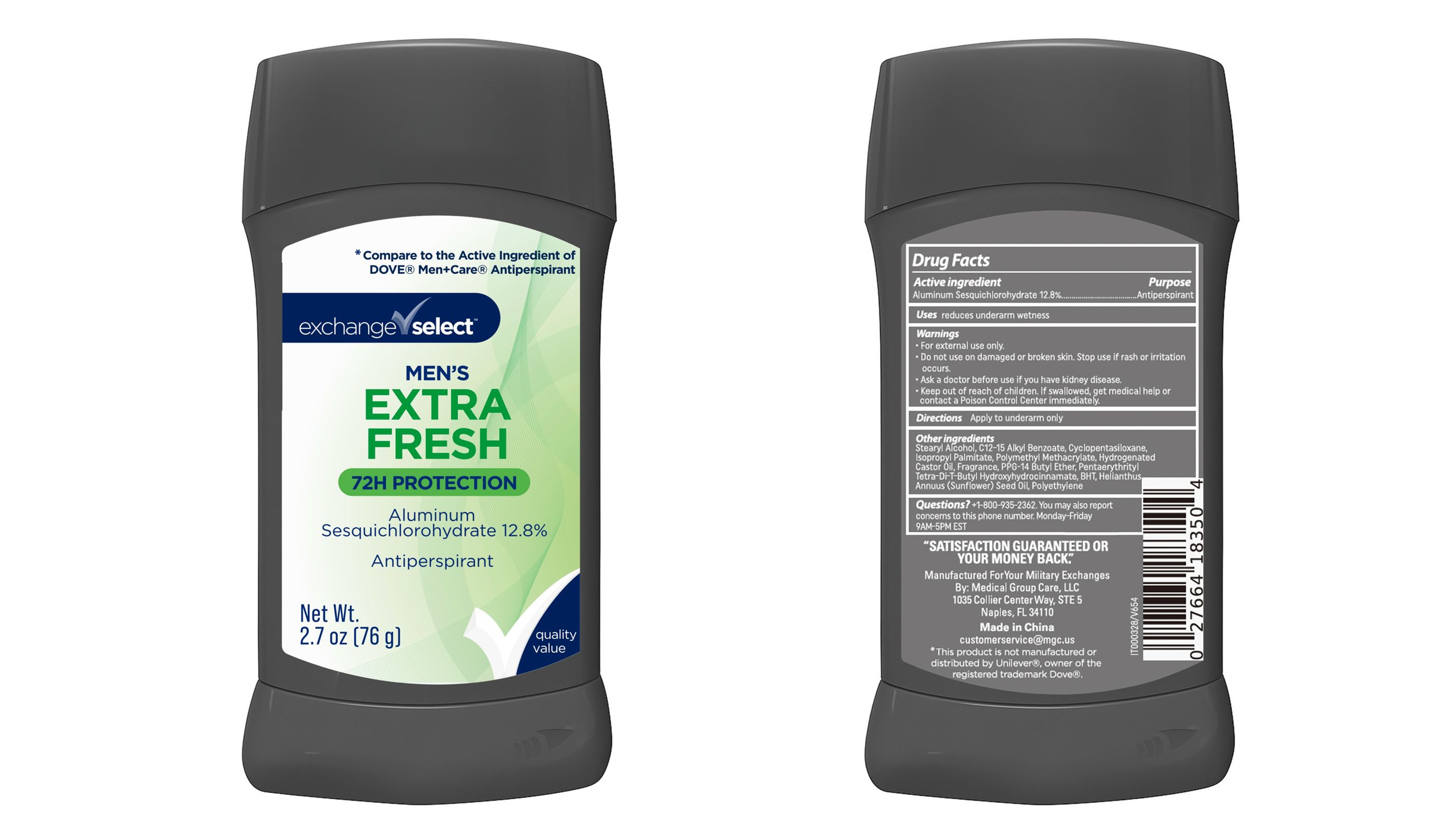 DRUG LABEL: Exchange Select Mens Extra Fresh Deodorant
NDC: 85161-223 | Form: STICK
Manufacturer: Longway Technology(Guangzhou) Co., Ltd
Category: otc | Type: HUMAN OTC DRUG LABEL
Date: 20251118

ACTIVE INGREDIENTS: ALUMINUM SESQUICHLOROHYDRATE 128 mg/1 g
INACTIVE INGREDIENTS: C12-15 ALKYL BENZOATE; CYCLOPENTASILOXANE; ISOPROPYL PALMITATE; POLY(METHYL METHACRYLATE; 450000 MW); HYDROGENATED CASTOR OIL; STEARYL ALCOHOL; PPG-14 BUTYL ETHER; PENTAERYTHRITYL TETRA-DI-T-BUTYL HYDROXYHYDROCINNAMATE; BHT; HELIANTHUS ANNUUS (SUNFLOWER) SEED OIL; POLYETHYLENE

Exchange Select Extra Fresh Deodorant

Drug Facts

Active ingredient

Aluminum Sesquichlorohydrate 12.8%

Purpose

Antiperspirant

Use

reduces underarm wetness

Warnings

For external use only

Do not use on damaged or broken skin. Stop use if rash or issitation occurs.

Ask a doctor before use if you have kidney disease

Keep out of reach of children. If swallowed, get medical help or contact a Poison Control Center immediately.

Directions

Apply to underarms only

Inactive ingredients

Stearyl Alcohol, C12-15 Alkyl Benzoate, Cyclopentasiloxane, Isopropyl Palmitate, Polymethyl Methacrylate, Hydrogenated Castor Oil, Fragrance, PPG-14 Butyl Ether, Pentaerythrityl Tetra-Di-T-Butyl Hydroxyhydrocinnamate, BHT, Helianthus Annuus (Sunflower) Seed Oil, Polyethylene

Questions?

+1-800-935-2362. You may also report concers to this phone

number. Monday-Friday, 9AM - 5PM EST.